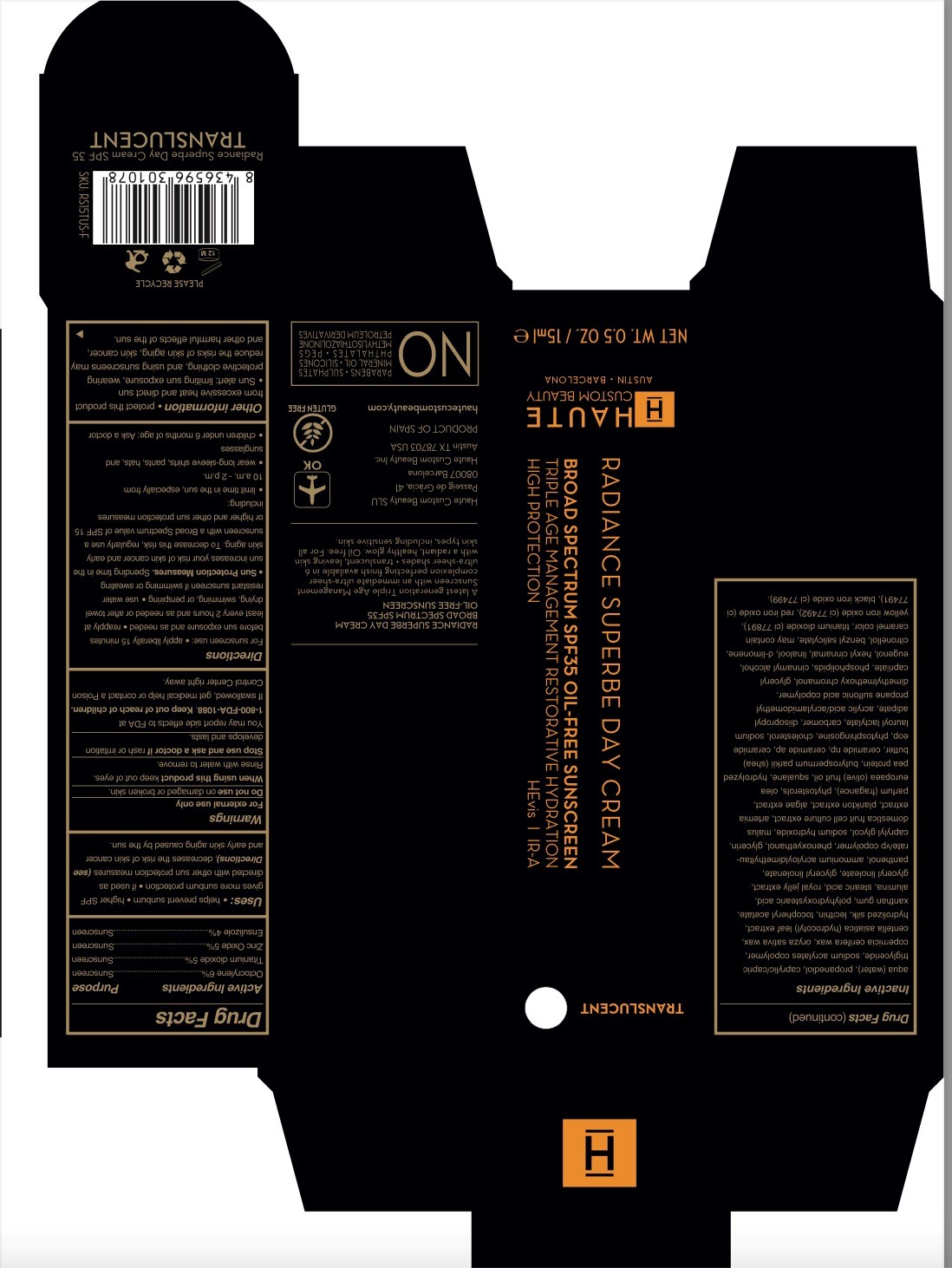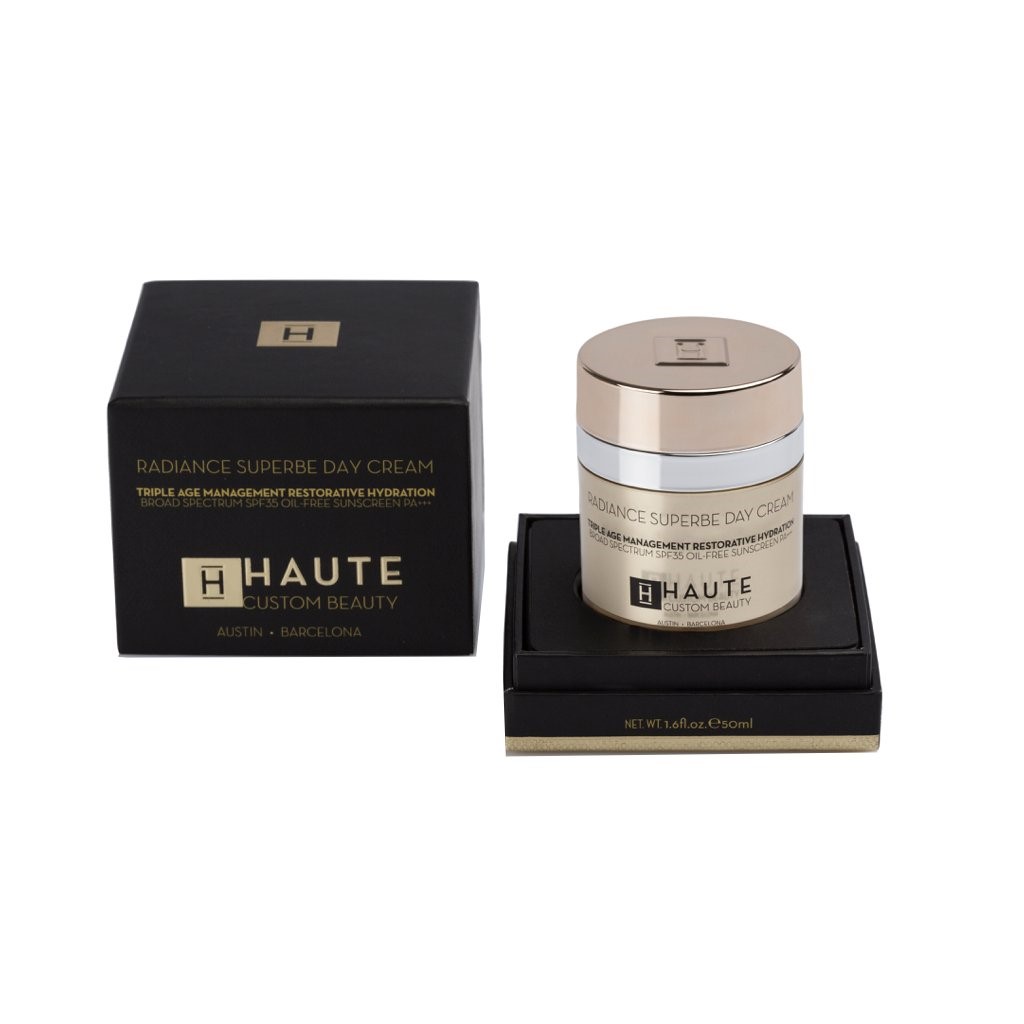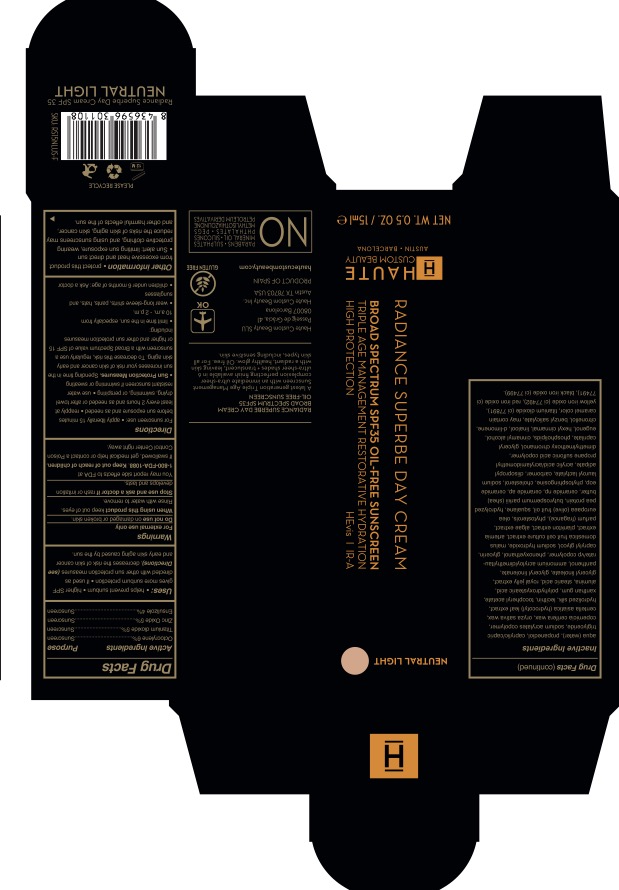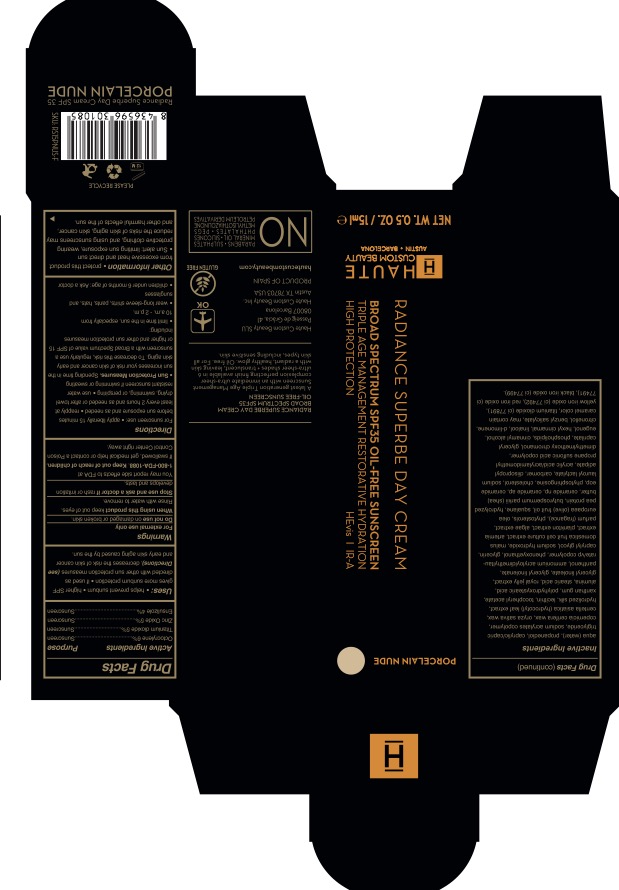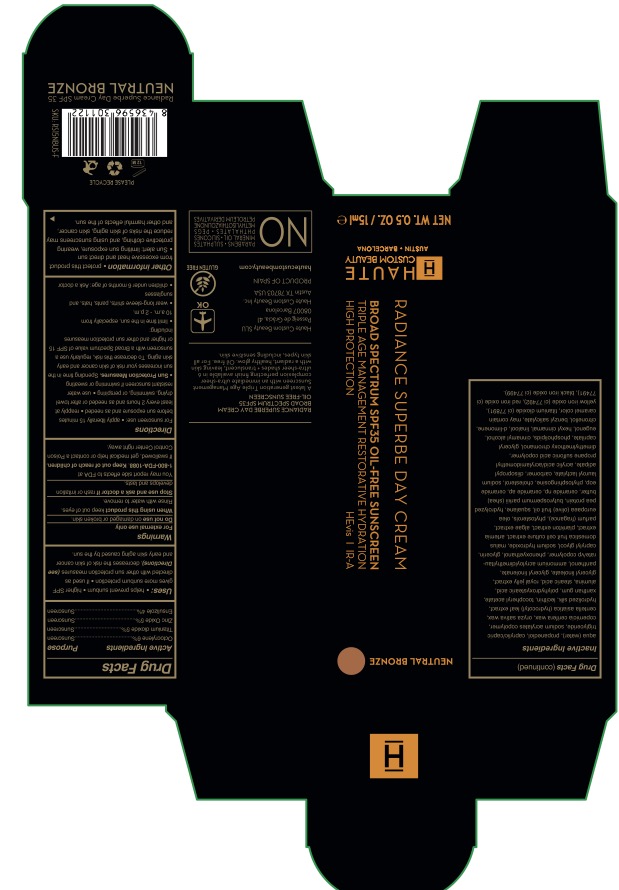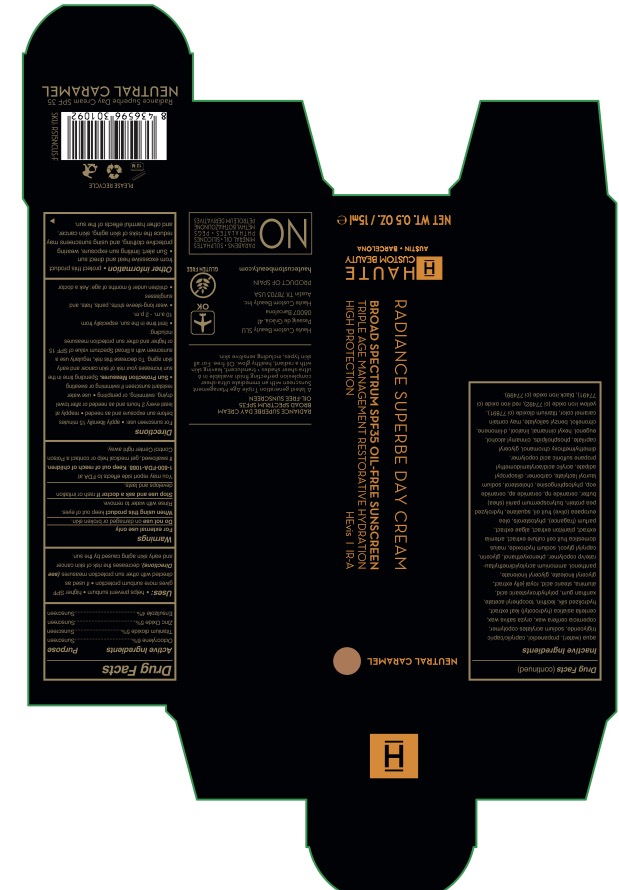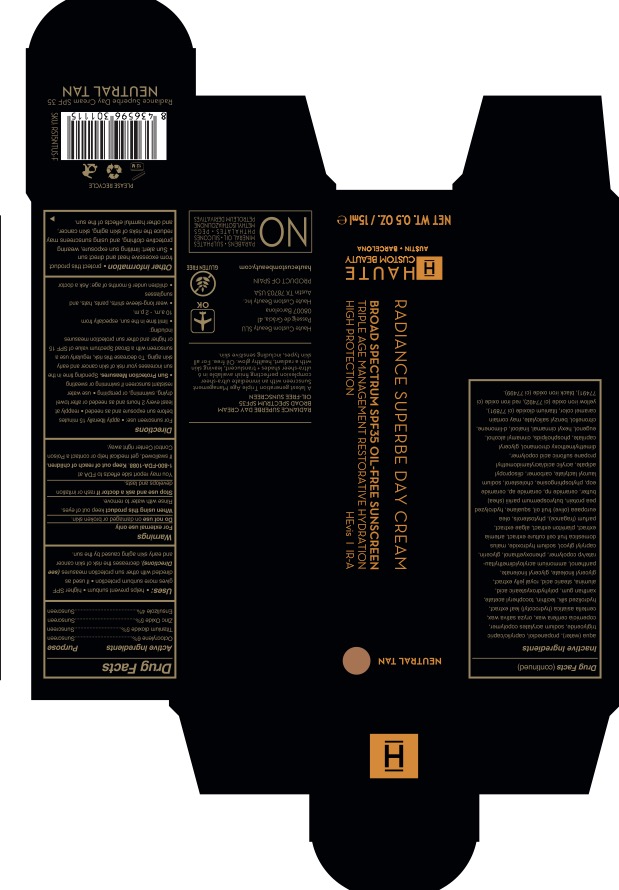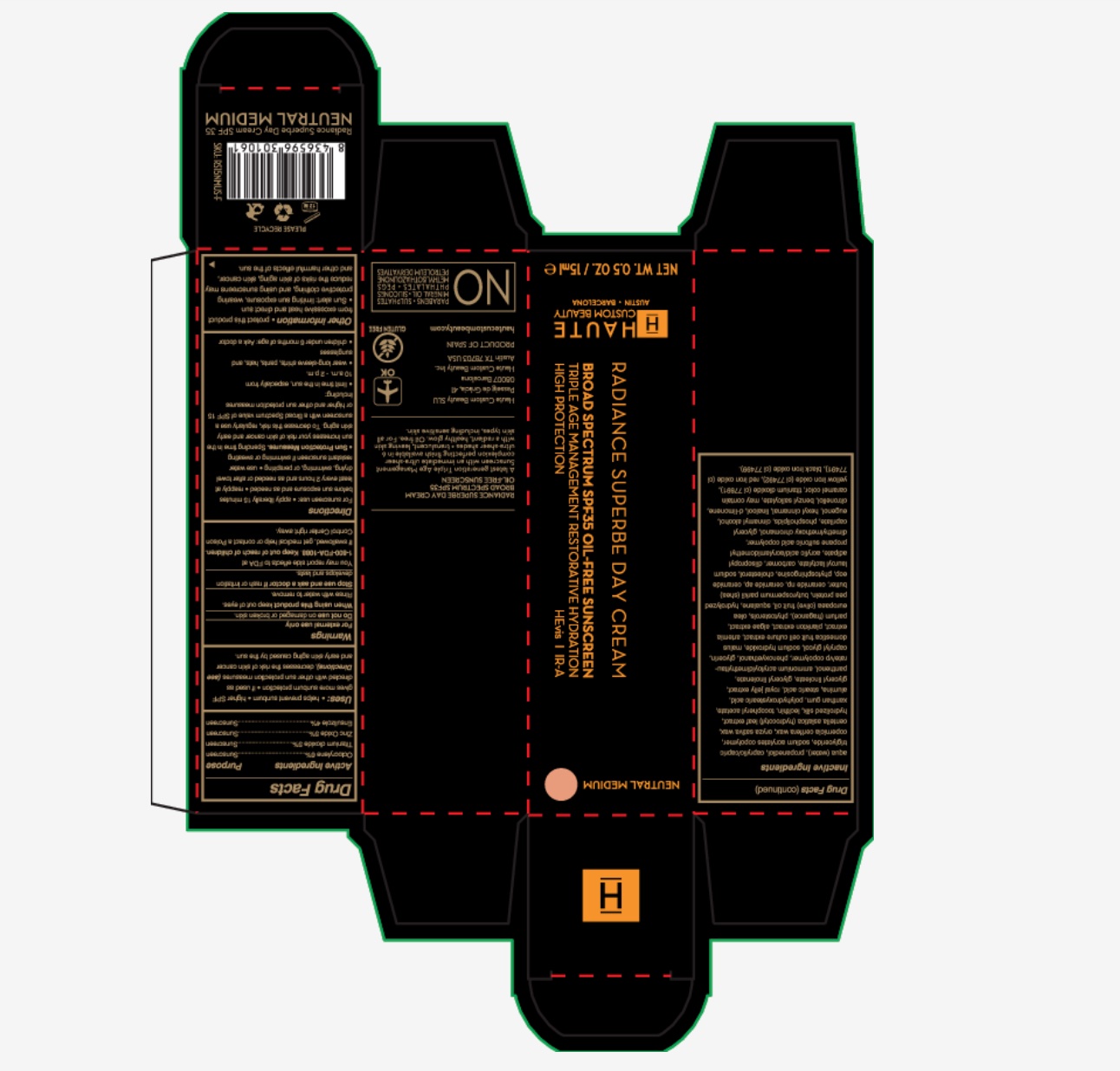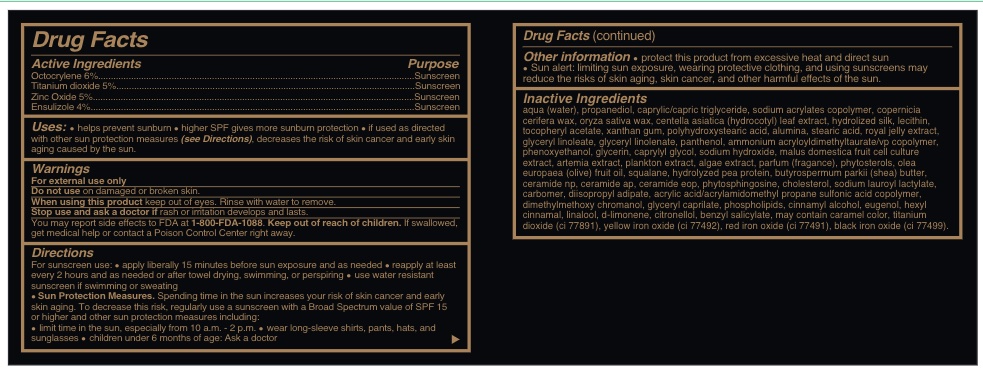 DRUG LABEL: Radiance Superbe Day Cream Nude
NDC: 72414-001 | Form: CREAM
Manufacturer: Haute Custom Beauty
Category: otc | Type: HUMAN OTC DRUG LABEL
Date: 20221105

ACTIVE INGREDIENTS: ENSULIZOLE 4 g/100 g; TITANIUM DIOXIDE 5 g/100 g; OCTOCRYLENE 6 g/100 g; ZINC OXIDE 5 g/100 g
INACTIVE INGREDIENTS: CERAMIDE AP; PHYTOSPHINGOSINE; GLYCERYL LINOLENATE; PEA PROTEIN; PHENOXYETHANOL; GLYCERIN; CERAMIDE NP; CINNAMYL ALCOHOL; BENZYL SALICYLATE; OLEA EUROPAEA FRUIT VOLATILE OIL; MALUS DOMESTICA WHOLE; ROYAL JELLY; PANTHENOL; CAPRYLIC/CAPRIC/LAURIC TRIGLYCERIDE; DIISOPROPYL ADIPATE; LINALOOL, (+)-; PROPANEDIOL; .ALPHA.-TOCOPHEROL ACETATE; POLYHYDROXYSTEARIC ACID (2300 MW); ALUMINUM HYDROXIDE; AMMONIUM ACRYLOYLDIMETHYLTAURATE/VP COPOLYMER; CAPRYLYL GLYCOL; CARNAUBA WAX; CHOLESTEROL; CENTELLA ASIATICA LEAF; SILK, ENZYME HYDROLYZED (1000 MW); LECITHIN, SOYBEAN; XANTHAN GUM; STEARIC ACID; GLYCERYL LINOLEATE; SODIUM 2-ACRYLAMIDO-2-METHYL-1-PROPANE SULFONATE/SODIUM ACRYLATE/N-ISOPROPYLACRYLAMIDE/TRIMETHYL(3-METHACRYLAMIDOPROPYL)AMMONIUM CHLORIDE COPOLYMER; DIMETHYLMETHOXY CHROMANOL; GLYCERYL CAPRYLATE; EGG PHOSPHOLIPIDS; LIMONENE, (+/-)-; .BETA.-CITRONELLOL, (+/-)-; SODIUM HYDROXIDE; SQUALANE; SHEA BUTTER; CERAMIDE EOS; SODIUM LAUROYL LACTYLATE; CARBOMER 980; EUGENOL; HEXYL CINNAMATE

Radiance Superbe Day Cream (Translucent and 6 tones)

Active Ingredients......sunscreen

Octocrylene 6%.........Sunscreen

Titanium dioxide 5%.........Sunscreen

Zinc oxide 5%.........Sunscreen

Ensulizole 4%..........Sunscreen

Inactive Ingredients

AQUA (WATER), PROPANEDIOL, CAPRYLIC/CAPRIC TRIGLYCERIDE, SODIUM ACRYLATES COPOLYMER, COPERNICIA CERIFERA WAX, ORYZA SATIVA WAX, CENTELLA ASIATICA (HYDROCOTYL) LEAF EXTRACT, HYDROLIZED SILK, LECITHIN, TOCOPHERYL ACETATE, XANTHAN GUM, POLYHYDROXYSTEARIC ACID, ALUMINA, STEARIC ACID, ROYAL JELLY EXTRACT, GLYCERYL LINOLEATE, GLYCERYL LINOLENATE, PANTHENOL, AMMONIUM ACRYLOYLDIMETHYLTAURATE/VP COPOLYMER, PHENOXYETHANOL, GLYCERIN, CAPRYLYL GLYCOL, SODIUM HYDROXIDE, MALUS DOMESTICA FRUIT CELL CULTURE EXTRACT, ARTEMIA EXTRACT, PLANKTON EXTRACT, ALGAE EXTRACT, PARFUM (FRAGANCE), PHYTOSTEROLS, OLEA EUROPAEA (OLIVE) FRUIT OIL, SQUALANE, HYDROLYZED PEA PROTEIN, BUTYROSPERMUM PARKII (SHEA) BUTTER, CERAMIDE NP, CERAMIDE AP, CERAMIDE EOP, PHYTOSPHINGOSINE, CHOLESTEROL, SODIUM LAUROYL LACTYLATE, CARBOMER, DIISOPROPYL ADIPATE, ACRYLIC ACID/ACRYLAMIDOMETHYL PROPANE SULFONIC ACID COPOLYMER, DIMETHYLMETHOXY CHROMANOL, GLYCERYL CAPRILATE, PHOSPHOLIPIDS, CARAMEL, CI 77891, CI 77492, CI 77491 , CI 77499 , CINNAMYL ALCOHOL, EUGENOL, HEXYL CINNAMAL, LINALOOL, d-LIMONENE, CITRONELLOL, BENZYL SALICYLATE.

Uses

helps prevent sunburn * higher SPF gives more sunburn protection * if used as directed with other sun protection measures (see Directions) decreases the risk of skin cancer and early skin aging caused by the sun.

Warnings

For external use only

Do not use on damaged or broken skin.

When using this product keep out of eyes. Rinse with water to remove.

Stop use and ask a doctor if rash or irratation develos and lasts.

You may report effects to FDA at 1-800-FDA-1088.

Keep out of reach of children. If swallowed, get medical help or contact a Poison Control Center right away.

Keep out of reach of children. If swallowed, get medical help or contact a Poison Control Center right away.

Directions

For suncreen use: *apply liberally 15 minutes before sun exposure and as needed * reapply at least every 2 hours and as needed or after towel drying, swimming, or perspiring. *. use water resistant sunscreen if swimming or sweating * Sun Protection measures. Spending time in the sun increases your risk of skin cancer and early skin aging. To decrease this risk, regularly use a sunscreen with a Broad Spectrum value of SPF 15 or higher and other sun protection measures including:

* limit time in th esun, especially from 10 a.m. - 2 p.m.

* wear long-sleeve shirts, pants, hats and sunglasses

*children under 6 months of age: Ask a doctor

Other information

Other information * protect this product from excessive heat and direct sun. * Sun alert: limiting sun exposure, wearing protective clothing, and using sunscreen may reduce the risks of skin aging, skin cancer, and other harmful effects of the sun.

Description

RADIANCE SUPERBE DAY CREAM

BROAD SPECTRUM SPF 35

OIL-FREE SUNSCREEN

A latest generation Triple Age Management Sunscreen with an immediate ultra-sheer complexion perfecting finish availalbe in 6 ultra-sheer shades + translucent, leaving skin with a radiant, healthy glow. Oil free, for all skin types, including sensitive skin.

Haute Custom Beauty SLU

Passeig de Gracia 41

08047 Barcelona

Haute Custom Beauty INC

Austin, TX 78703 USA

PRODUCT OF SPAIN

www.hautecustombeauty.com

Airplane image OK

Gluten Free

No: parabens, sulphates, mineral oil, silicons, phthalates, PEGS, methysilothazzolinone, petroleum derivatives